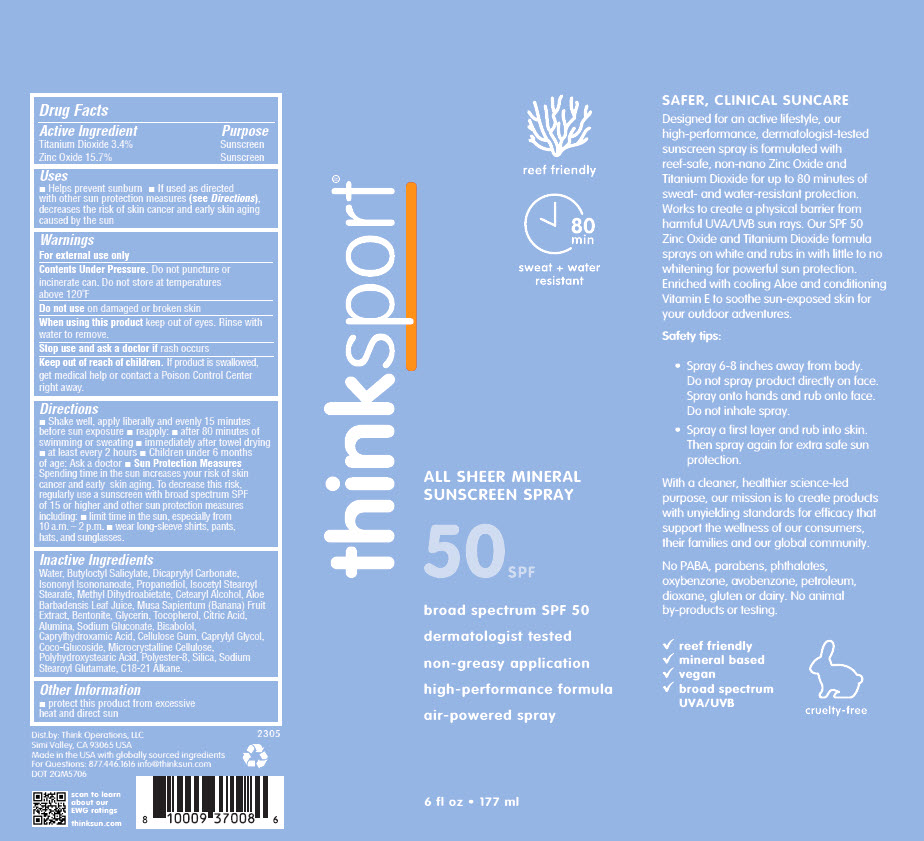 DRUG LABEL: Thinksport Mineral 
NDC: 60781-4708 | Form: AEROSOL
Manufacturer: thinkOperations,LLC
Category: otc | Type: HUMAN OTC DRUG LABEL
Date: 20230601

ACTIVE INGREDIENTS: ZINC OXIDE 157 mg/1 mL; TITANIUM DIOXIDE 34 mg/1 mL
INACTIVE INGREDIENTS: WATER; BUTYLOCTYL SALICYLATE; DICAPRYLYL CARBONATE; ISONONYL ISONONANOATE; PROPANEDIOL; ISOCETYL STEAROYL STEARATE; METHYL DEHYDROABIETATE; CETOSTEARYL ALCOHOL; ALOE VERA LEAF; BANANA; BENTONITE; GLYCERIN; .ALPHA.-TOCOPHEROL; CITRIC ACID MONOHYDRATE; ALUMINUM OXIDE; SODIUM GLUCONATE; .ALPHA.-BISABOLOL, (+)-; CAPRYLHYDROXAMIC ACID; CARBOXYMETHYLCELLULOSE; CAPRYLYL GLYCOL; COCO GLUCOSIDE; MICROCRYSTALLINE CELLULOSE; POLYHYDROXYSTEARIC ACID (2300 MW); POLYESTER-8 (1400 MW, CYANODIPHENYLPROPENOYL CAPPED); SILICON DIOXIDE; SODIUM STEAROYL GLUTAMATE; C18-C21 ALKANE

Thinksport® Mineral
SPF 50

Drug Facts

ACTIVE INGREDIENT

Active Ingredient | Purpose
Titanium Dioxide 3.4% | Sunscreen
Zinc Oxide 15.7% | Sunscreen

Uses

- Helps prevent sunburn
- If used as directed with other sun protection measures (see Directions), decreases the risk of skin cancer and early skin aging caused by the sun

Warnings

For external use only

Contents Under Pressure. Do not puncture or incinerate can. Do not store at temperatures above 120°F

Do not use on damaged or broken skin

When using this product keep out of eyes. Rinse with water to remove.

Stop use and ask a doctor if rash occurs

Keep out of reach of children. If product is swallowed, get medical help or contact a Poison Control Center right away.

Directions

- Shake well, apply liberally and evenly 15 minutes before sun exposure
- reapply:
  - after 80 minutes of swimming or sweating
  - immediately after towel drying
  - at least every 2 hours
- Children under 6 months of age: Ask a doctor
- Sun Protection Measures
  Spending time in the sun increases your risk of skin cancer and early skin aging. To decrease this risk, regularly use a sunscreen with broad spectrum SPF of 15 or higher and other sun protection measures including:
  - limit time in the sun, especially from 10 a.m. – 2 p.m.
  - wear long-sleeve shirts, pants, hats, and sunglasses.

Inactive Ingredients

Water, Butyloctyl Salicylate, Dicaprylyl Carbonate, Isononyl Isononanoate, Propanediol, Isocetyl Stearoyl Stearate, Methyl Dihydroabietate, Cetearyl Alcohol, Aloe Barbadensis Leaf Juice, Musa Sapientum (Banana) Fruit Extract, Bentonite, Glycerin, Tocopherol, Citric Acid, Alumina, Sodium Gluconate, Bisabolol, Caprylhydroxamic Acid, Cellulose Gum, Caprylyl Glycol, Coco-Glucoside, Microcrystalline Cellulose, Polyhydroxystearic Acid, Polyester-8, Silica, Sodium Stearoyl Glutamate, C18-21 Alkane.

Other Information

- protect this product from excessive heat and direct sun

For Questions

877.446.1616

Dist.by: Think Operations, LLC
Simi Valley, CA 93065 USA

PRINCIPAL DISPLAY PANEL - 177 ml Canister Label

thinksport®

reef friendly

80
min
sweat + water
resistant

ALL SHEER MINERAL
SUNSCREEN SPRAY

50 SPF

broad spectrum SPF 50
dermatologist tested
non-greasy application
high-performance formula
air-powered spray

6 fl oz • 177 ml